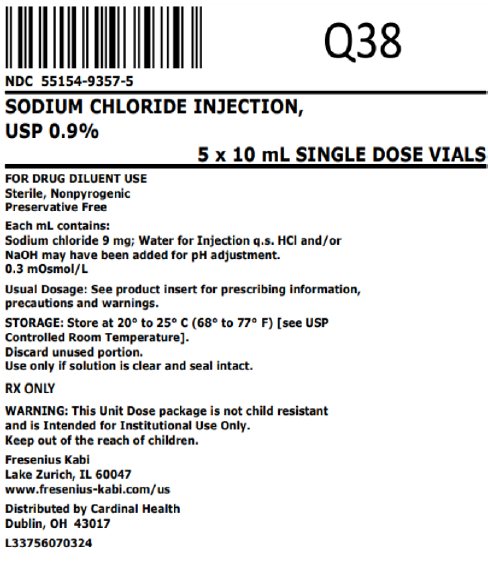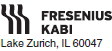 DRUG LABEL: Sodium Chloride
NDC: 55154-9357 | Form: INJECTION
Manufacturer: Cardinal Health 107, LLC
Category: prescription | Type: HUMAN PRESCRIPTION DRUG LABEL
Date: 20251029

ACTIVE INGREDIENTS: SODIUM CHLORIDE 9 mg/1 mL
INACTIVE INGREDIENTS: WATER

Sodium Chloride Injection, USP
0.9%

DESCRIPTION:

This preparation is designed solely for parenteral use only after addition of drugs that require dilution or must be dissolved in an aqueous vehicle prior to injection.

Sodium Chloride Injection, USP, 0.9% is a sterile, nonpyrogenic solution. The osmolarity is 0.300 mOsmol/mL (calculated).

Each mL contains: Sodium chloride 9 mg; Water for Injection q.s. It contains no bacteriostat, antimicrobial agent or added buffer and is supplied only in single dose containers. Hydrochloric acid and/or sodium hydroxide may have been added for pH adjustment (pH 4.5-7.0).

Sodium chloride occurs as colorless cubic crystals or white crystalline powder and has a saline taste. Sodium chloride is freely soluble in water. It is soluble in glycerin and slightly soluble in alcohol.

The empirical formula for sodium chloride is NaCl and the molecular weight is 58.44.

CLINICAL PHARMACOLOGY:

Sodium chloride in water dissociates to provide sodium (Na^+) and chloride (Cl—) ions. These ions are normal constituents of the body fluids (principally extracellular) and are essential for maintaining electrolyte balance.

The distribution and excretion of sodium (Na^+) and chloride (Cl—) are largely under the control of the kidney which maintains a balance between intake and output.

The small volume of fluid and amount of sodium chloride provided by Sodium Chloride Injection, USP, 0.9%, when used only as an isotonic vehicle for parenteral injection of drugs, is unlikely to exert a significant effect on fluid and electrolyte balance except possibly in neonates and very small infants.

Water is an essential constituent of all body tissues and accounts for approximately 70% of total body weight. Average normal adult daily requirement ranges from two to three liters (1 to 1.5 liters each for insensible water loss by perspiration and urine production).

Water balance is maintained by various regulatory mechanisms. Water distribution depends primarily on the concentration of electrolytes in the body compartments and sodium (Na^+) plays a major role in maintaining physiologic equilibrium.

INDICATIONS AND USAGE:

This parenteral preparation is indicated only for diluting or dissolving drugs for intravenous, intramuscular, or subcutaneous injection, according to instructions of the manufacturer of the drug to be administered.

PRECAUTIONS:

Consult the manufacturer's instructions for choice of vehicle, appropriate dilution or volume for dissolving the drugs to be injected, including the route and rate of injection. Inspect reconstituted (diluted or dissolved) drugs for clarity (if soluble) and freedom from unexpected precipitation or discoloration prior to administration.

Pregnancy

Animal reproduction studies have not been conducted with Sodium Chloride Injection, USP, 0.9%. It is also not known whether Sodium Chloride Injection containing additives can cause fetal harm when administered to a pregnant woman or can affect reproduction capacity. Sodium Chloride Injection, USP, 0.9% containing additives should be given to a pregnant woman only if clearly needed.

Pediatric Use

The safety and effectiveness in the pediatric population are based on the similarity of the clinical conditions of the pediatric and adult populations. In neonates or very small infants the volume of fluid may affect fluid and electrolyte balance.

Drug Interactions

Some drugs for injection may be incompatible in a given vehicle, or when combined in the same vehicle or in a vehicle containing benzyl alcohol. Consult with pharmacist, if available.

Use aseptic technique for single or multiple entry and withdrawal from all containers.

When diluting or dissolving drugs, mix thoroughly and use promptly.

Do not store reconstituted solutions of drugs for injection unless otherwise directed by the manufacturer of the solute.

Do not use unless the solution is clear and seal intact. Do not reuse single dose containers, discard unused portion.

ADVERSE REACTIONS:

Reactions which may occur because of this solution, added drugs or the technique of reconstitution or administration include febrile response, local tenderness, abscess, tissue necrosis or infection at the site of injection, venous thrombosis or phlebitis extending from the site of injection and extravasation.

If an adverse reaction does occur, discontinue the infusion, evaluate the patient, institute appropriate countermeasures and, if possible, retrieve and save the remainder of the unused vehicle for examination.

OVERDOSAGE:

Use only as a diluent or solvent. This parenteral preparation is unlikely to pose a threat of carbohydrate, sodium chloride or fluid overload except possibly in neonates or very small infants. In the event these should occur, reevaluate the patient and institute appropriate corrective measures. (See PRECAUTIONS and ADVERSE REACTIONS).

DOSAGE AND ADMINISTRATION:

The volume of the preparation to be used for diluting or dissolving any drug for injection, is dependent on the vehicle concentration, dose and route of administration as recommended by the manufacturer.

This parenteral should be inspected visually for particulate matter and discoloration prior to administration, whenever solution and container permit. See PRECAUTIONS.

HOW SUPPLIED:

Sodium Chloride Injection, USP, 0.9%, preservative free, is available as follows:

Unit of Sale

Overbagged with 5 x 10 mL Single Dose vial in each bag, NDC 55154-9357-5

WARNING: This Unit Dose package is not child resistant and is Intended for Institutional Use Only. Keep this and all drugs out of the reach of children.

Preservative Free. Discard unused portion.

Use only if solution is clear and seal intact.

Store at 20º to 25ºC (68º to 77ºF) [see USP Controlled Room Temperature]

www.fresenius-kabi.com/us

Distributed By:

Cardinal Health

Dublin, OH 43017

L33756070324

45764F

Revised: November 2020

Package/Label Display Panel

NDC 55154-9357-5

SODIUM CHLORIDE INJECTION,

USP 0.9%

5 x 10 mL SINGLE DOSE VIALS